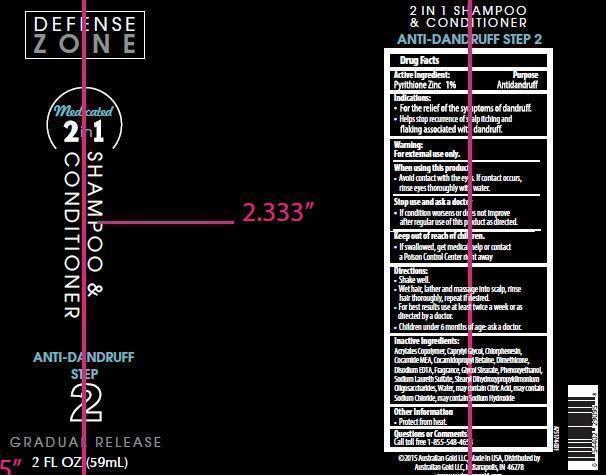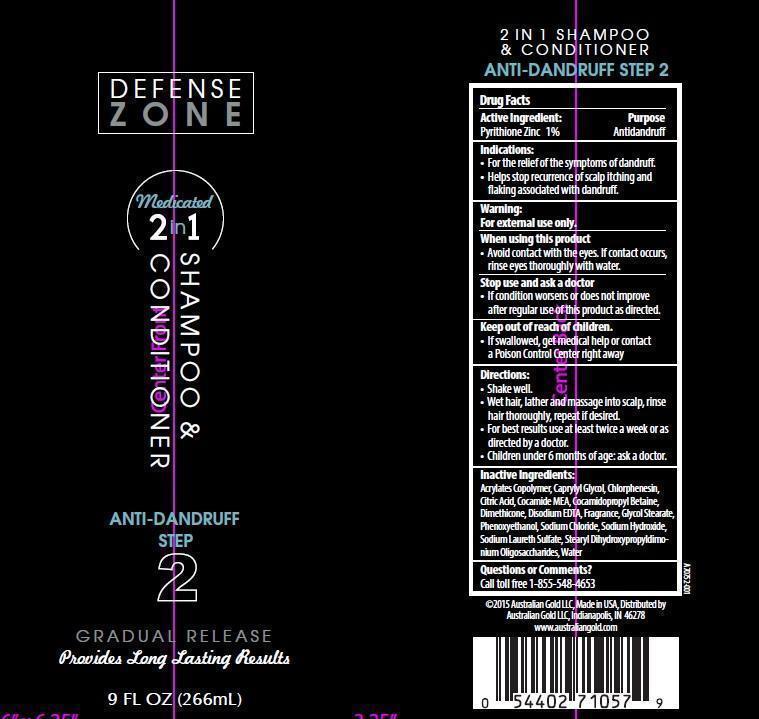 DRUG LABEL: Australian Gold Defense Zone
NDC: 58443-0180 | Form: SHAMPOO
Manufacturer: Prime Enterprises, Inc.
Category: otc | Type: HUMAN OTC DRUG LABEL
Date: 20200117

ACTIVE INGREDIENTS: PYRITHIONE ZINC 10.32 mg/1 mL
INACTIVE INGREDIENTS: CARBOMER INTERPOLYMER TYPE A (55000 CPS); CAPRYLYL GLYCOL; CHLORPHENESIN; CITRIC ACID ACETATE; COCO MONOETHANOLAMIDE; COCAMIDOPROPYL BETAINE; DIMETHICONE; EDETATE DISODIUM; GLYCOL STEARATE; PHENOXYETHANOL; SODIUM CHLORIDE; SODIUM HYDROXIDE; SODIUM LAURETH SULFATE; GUAR HYDROXYPROPYLTRIMONIUM CHLORIDE (1.7 SUBSTITUENTS PER SACCHARIDE); WATER

Active ingredients

Pyrithione Zinc 1%

Purpose

Antidanruff

Uses

- For the relief of the symptoms of dandruff.
- Helps Stop recurrence of scalp itching and flaking associated with dandruff.

Warnings

OTHER SAFETY INFORMATION

For external use only.

When using this product

- Avoid contact with the eyes. If contact occurs, rinse eyes thorougly with water.

Stop use and ask a doctor if

- If Condition worsens or does not improve after regular use of this product as directed

Keep out of reach of children.

- If product is swallowed, get medical help or contact a Poison Control Center right away.

Directions

- Shake well
- Wet hair, lather and massage into scalp, rinse hair thoroughly, repeat if desired,
- For best results use at least twice a week or as directed by a doctor.
- Children under 6 months of age: ask a doctor.

Inactive Ingrediets:

Acrylates Copolymer, Caprylyl Glycol, Chlorphenesin, Citric Acid, Cocamide MEA, Cocamidopropyl Betaine, Dimethicone, Disodium EDTA, Fragrance, Glycol Stearate, Phenoxyethanol, Sodium Chloride, Sodium Hydroxide, Sodium Laureth Sulfate, Stearyl Dihydroxypropyldimonium Oligosaccharides, Water

Questions or Comments?

Call toll free 1-855-548-4653

PRINCIPAL DISPLAY PANEL - 266 mL Bottle Label PRINCIPAL DISPLAY PANEL - 59 mL Bottle Label

Defense

Zone

Medicated 2 in 1

Shampoo &

Conditioner

Anti-Dandruff

Step

2

Gradual Release

Provides Long Lating Results

9 FL OZ (266mL)

Defense

Zone

Medicated

2 in 1

Shampoo &

Conditioner

Anti-Dandruff

Step

2

Gradual Release

2 FL OZ (59mL)

PACKAGE LABEL

Defense

Zone

Medicated

2 in 1

Shampoo &

Conditioner

Anti-Dandruff

Step

2

Gradual Release

2 FL OZ (59mL)